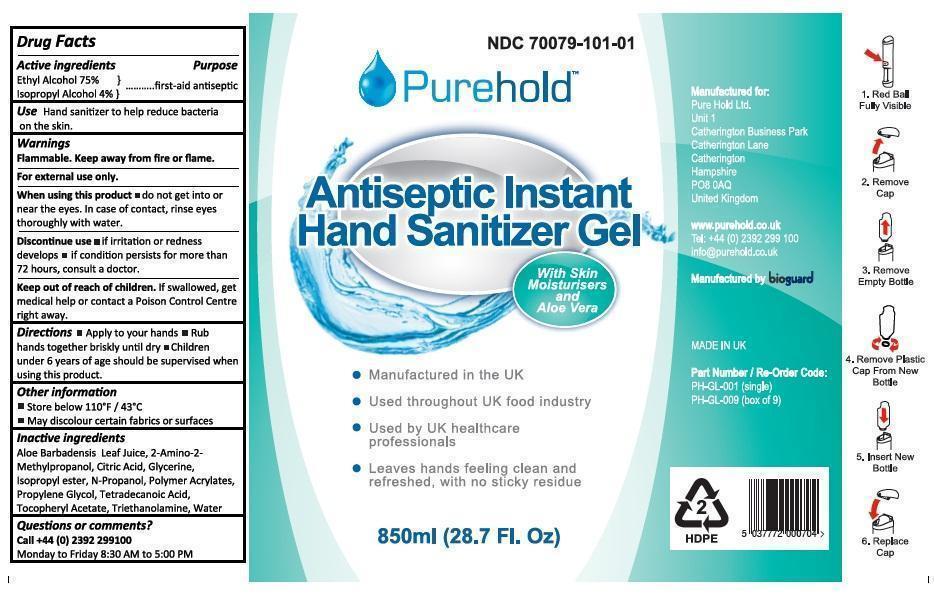 DRUG LABEL: Purehold Antiseptic Instant Hand Sanitizer
NDC: 70079-101 | Form: GEL
Manufacturer: Pure Hold Ltd
Category: otc | Type: HUMAN OTC DRUG LABEL
Date: 20250807

ACTIVE INGREDIENTS: ALCOHOL 75 mL/100 mL; ISOPROPYL ALCOHOL 4 mL/100 mL
INACTIVE INGREDIENTS: ALOE VERA LEAF; AMINOMETHYLPROPANOL; CARBOMER INTERPOLYMER TYPE A (ALLYL SUCROSE CROSSLINKED); ISOPROPYL MYRISTATE; CITRIC ACID MONOHYDRATE; GLYCERIN; PROPYL ALCOHOL; PROPYLENE GLYCOL; MYRISTIC ACID; .ALPHA.-TOCOPHEROL ACETATE; TROLAMINE; WATER

Purehold Antiseptic Instant Hand Sanitizer Gel

Active ingredients

Ethyl Alcohol 75%

Isopropyl Alchool 4%

Purpose

first-aid antiseptic

Keep out of reach of children. If swallowed, get medical help or contact a Poison Control Centre right away.

INDICATIONS AND USAGE

Use Hand sanitizer to help reduce bacteria on the skin

Warnings

Flammable. Keep away from fire or flame.

For external use only.

When using this product • do not get into or near the eyes. In case of contact, rinse eyes thoroughly with water.

Discontinue use • if irritation or redness develops • if condition persists for more than 72 hours, consult a doctor.

DOSAGE AND ADMINISTRATION

Directions • Apply to your hands • Rub hands together briskly until dry • Children under 6 years of age should be supervised when using this product.

Inactive ingredients

Aloe Barbadensis leaf juice, 2-Amino-2-Methylpropanol, Citric acid, Glycerine, Isopropyl ester, N-Propanol, Polymer acrylates, Propylene Glycol, Tetradecanoic Acid, Tocopheryl Acetate, Triethanolamine, Water.

Other information

• Store below 110°F / 43°C

• May discolour certain fabrics or surfaces

Questions or comments?

Call +44 (0) 2392 299100

Monday to Friday 8.30 AM to 5.00 PM

Manufacture for:

Pure Hold Ltd.

Unit 1

Catherington Business Park

Catherington Lane

Catherington

Hampshire

PO8 0AQ

United Kingdom

www.purehold.co.uk

Tel: +44 (0) 2392 299 100

info@purehold.co.uk

Manufactured by bioguard